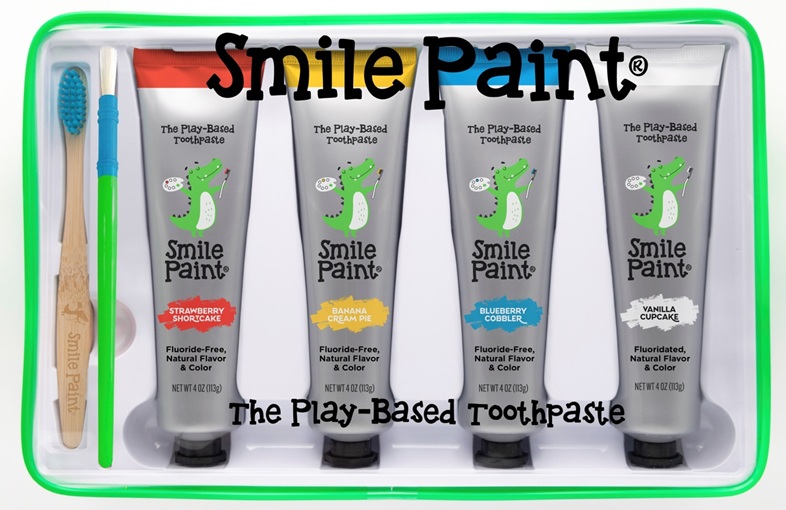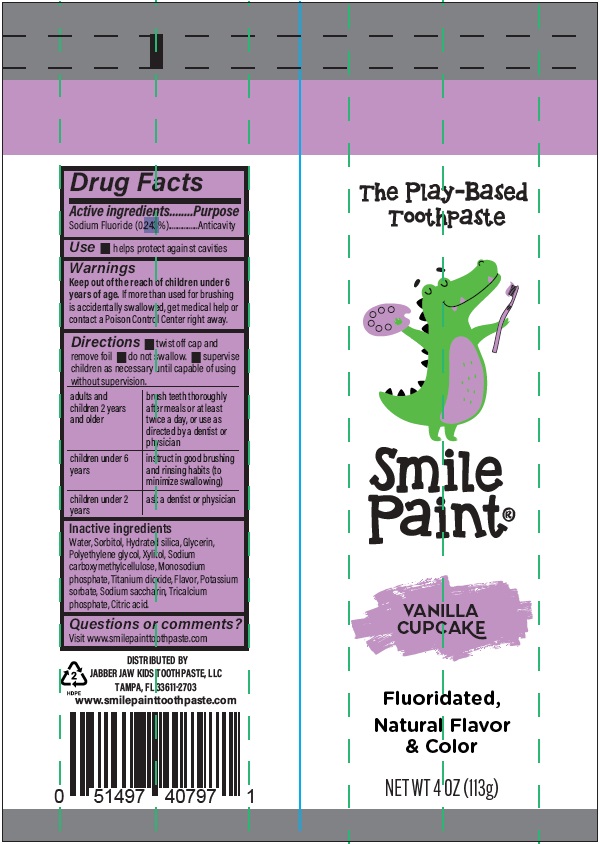 DRUG LABEL: Smile Paint
NDC: 87245-001 | Form: KIT | Route: DENTAL
Manufacturer: JABBER JAW KIDS TOOTHPASTE LLC
Category: otc | Type: HUMAN OTC DRUG LABEL
Date: 20260102

ACTIVE INGREDIENTS: SODIUM FLUORIDE 0.24 g/100 g
INACTIVE INGREDIENTS: WATER; SORBITOL; HYDRATED SILICA; GLYCERIN; POLYETHYLENE GLYCOL, UNSPECIFIED; XYLITOL; CARBOXYMETHYLCELLULOSE SODIUM; SODIUM PHOSPHATE, MONOBASIC, UNSPECIFIED FORM; TITANIUM DIOXIDE; POTASSIUM SORBATE; SACCHARIN SODIUM; TRICALCIUM PHOSPHATE; CITRIC ACID

Jabber Jaw Smile Paint Sodium Fluoride Kit

Active ingredients

Sodium Fluoride (0.24%)

Purpose Anticavity

INDICATIONS AND USAGE

Uses ■ helps protect against cavities

Warnings

KEEP OUT OF REACH OF CHILDREN

Keep out of the reach of children under 6 years of age.

If more than used for brushing is accidentally swallowed, get

medical help or contact a Poison Control Center right away.

DOSAGE AND ADMINISTRATION

Directions ■twist off cap and remove foil ■do not swallow ■supervise children

as necessary until capable of using without supervision.

adults and children 2 years and older | brush teeth thoroughly after meals or at least twice a day, or use as directed by a dentist or physician
children under 6 years | instruct in good brushing and rinsing habits (to minimize swallowing)
children under 2 years | ask a dentist or physician

Inactive ingredients

Water, Sorbitol, Hydrated Silica, Glycerin,
Polyethylene glycol, Xylitol, Sodium
Carboxymethylcellulose, Monosodium
phosphate, Titanium dioxide, Flavor, Potassium
sorbate, Sodium saccharin, Tricalcium
phosphate, Citric acid

Questions or comments?

Visit www.smilepainttoothpaste.com

Package Labeling:

-------------------------------------------------------------------

The Play-Based

Toothpaste

Smile Paint®

Vanilla Cupcake

Fluoridated,

Natural Flavor & Color

NET WT 4 OZ (113g)

DISTRIBUTED BY

JABBER JAW KIDS TOOTHPASTE, LLC

TAMPA, FL 33611-2703

www.smilepainttoothpaste.com

Kit

Tube

res